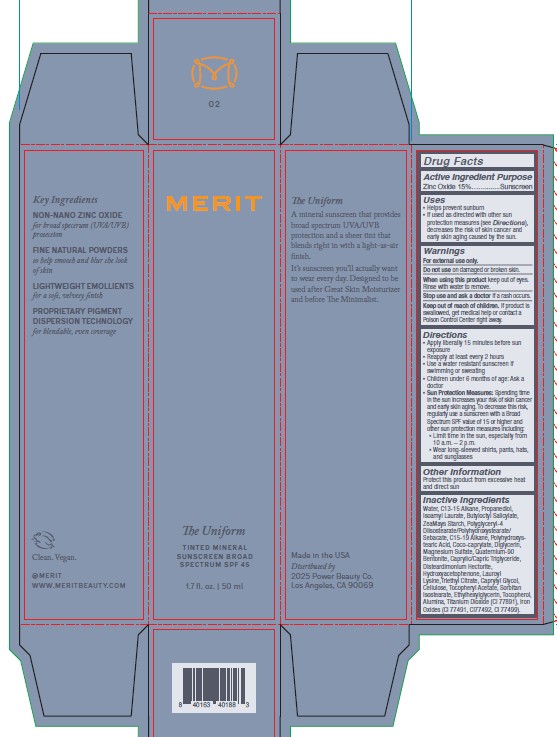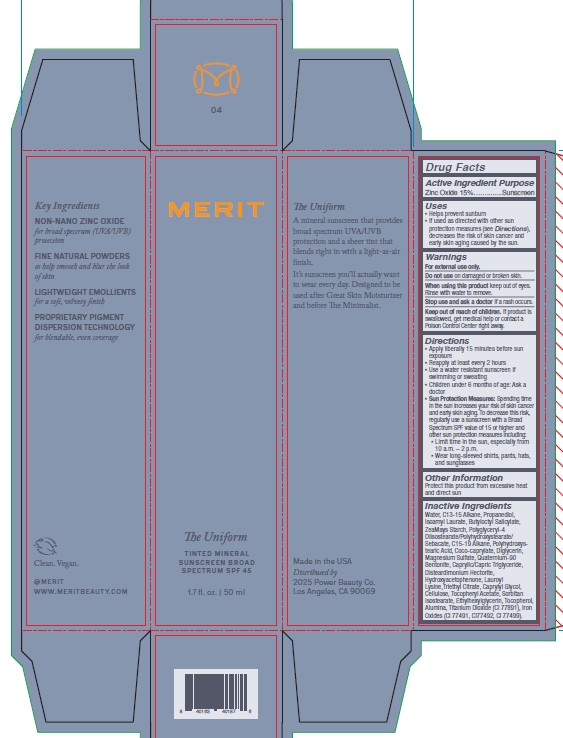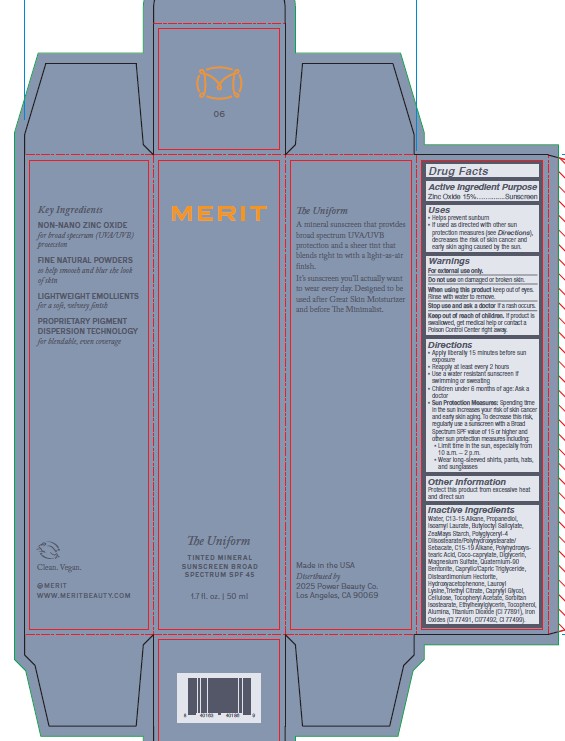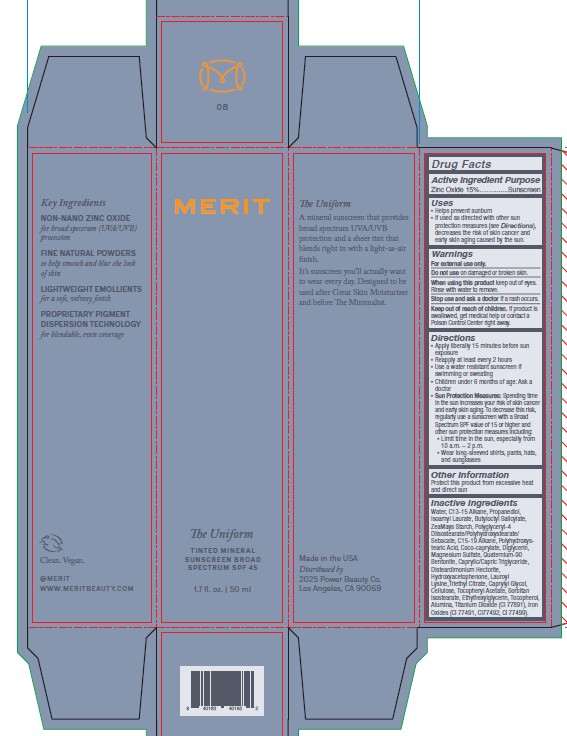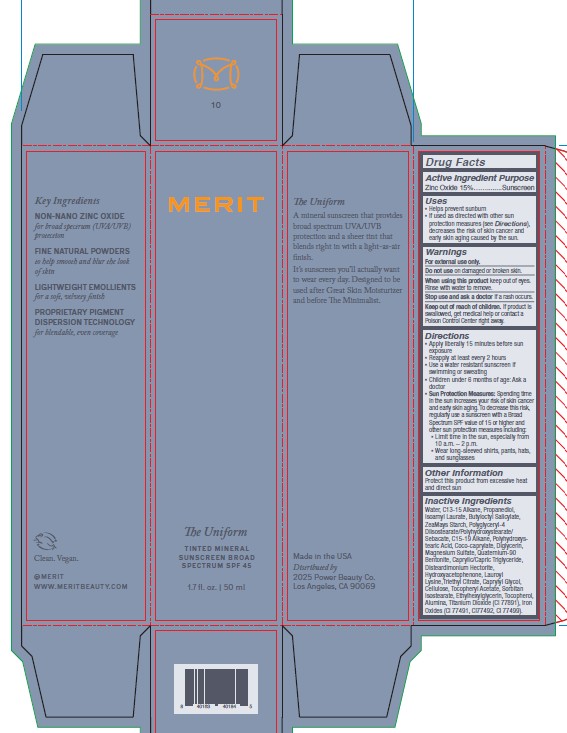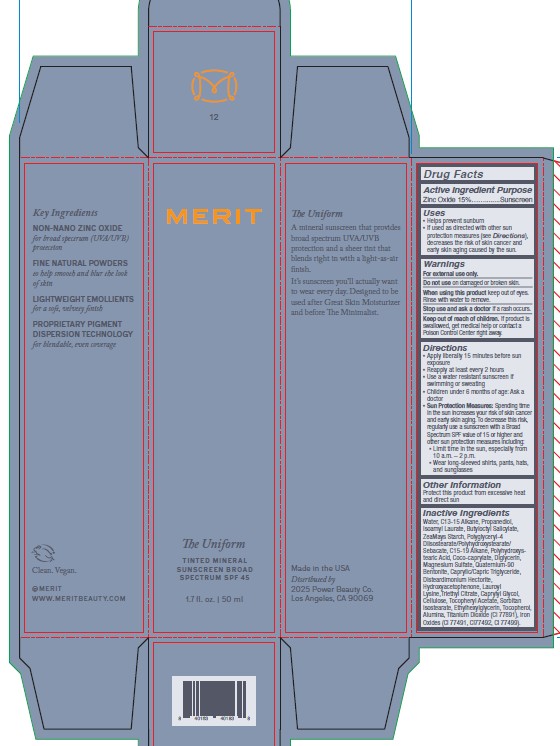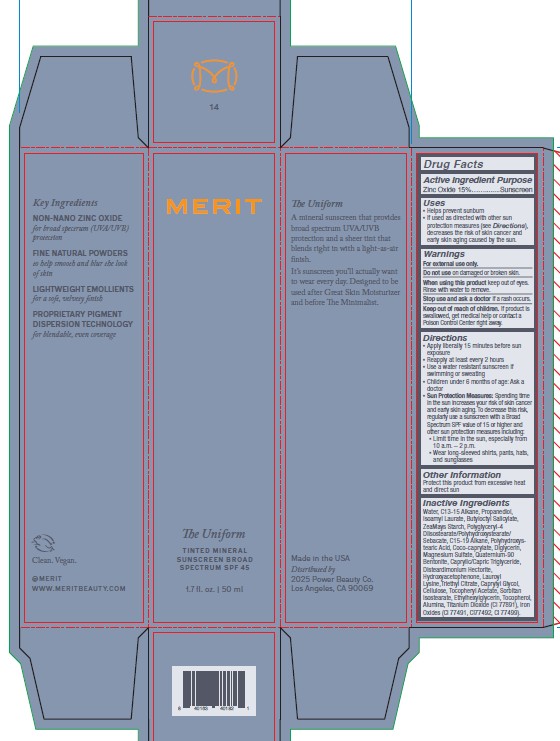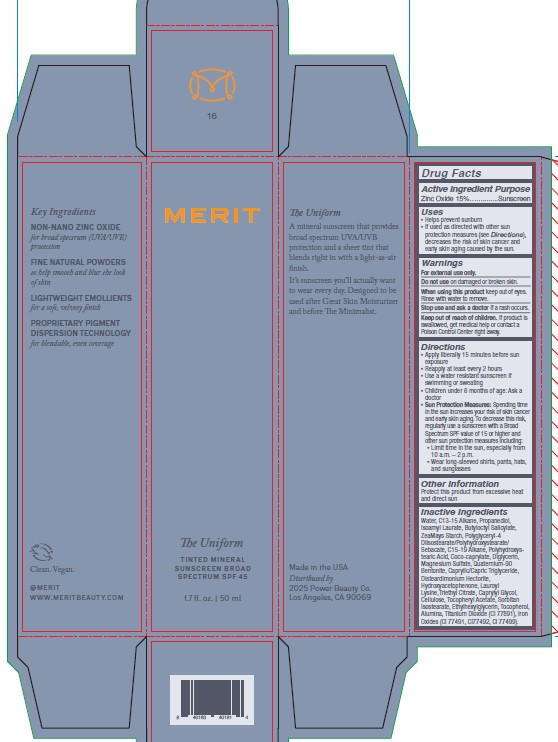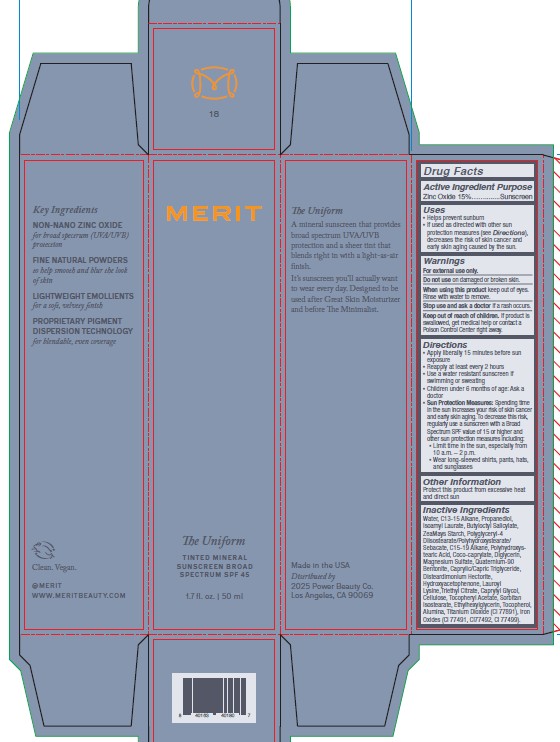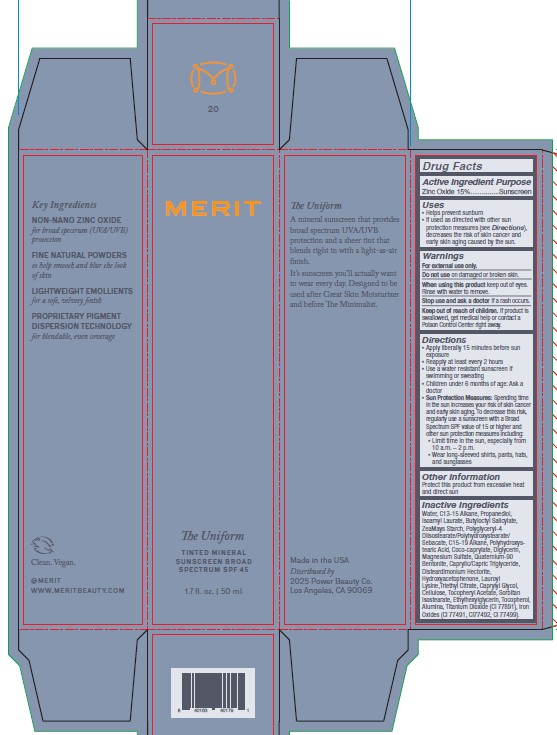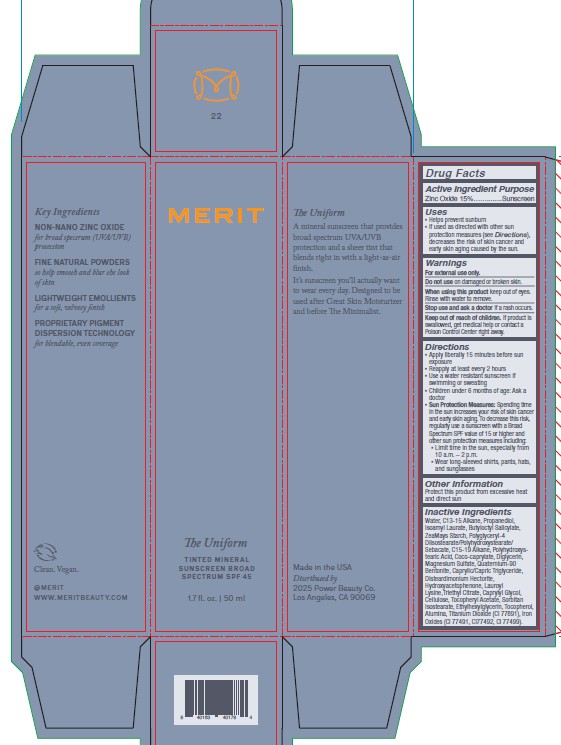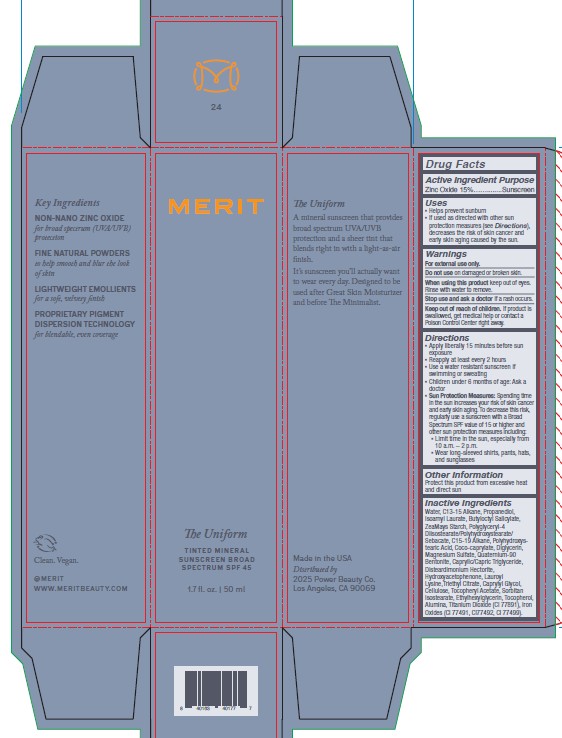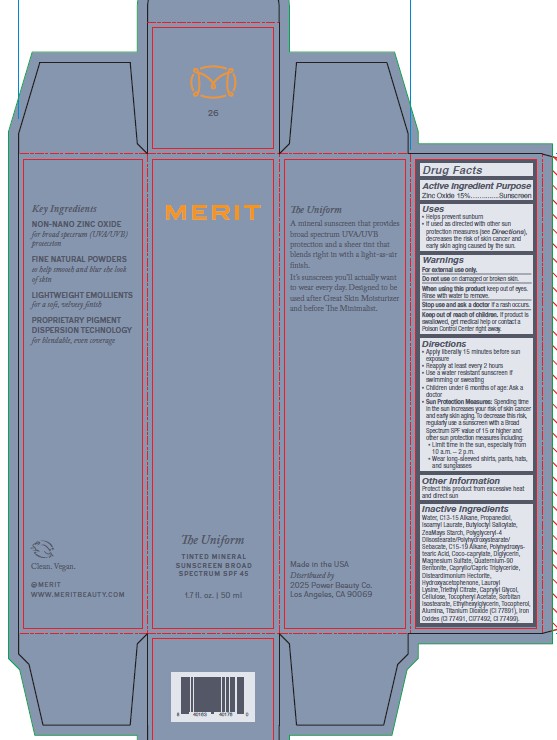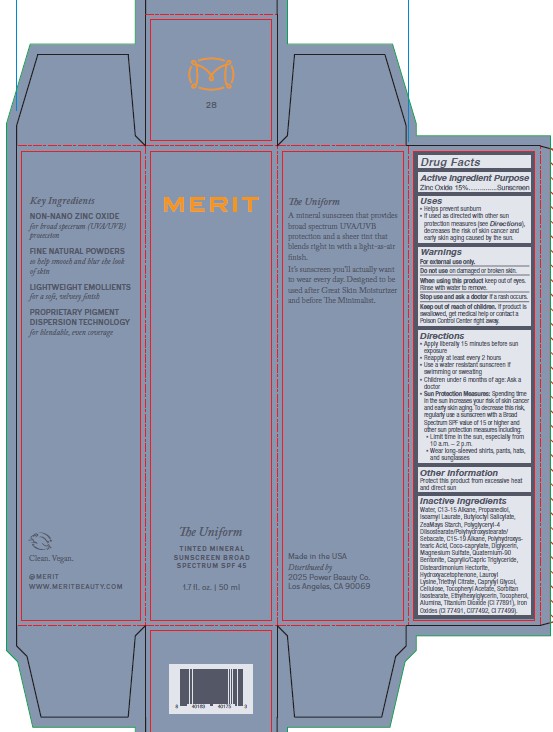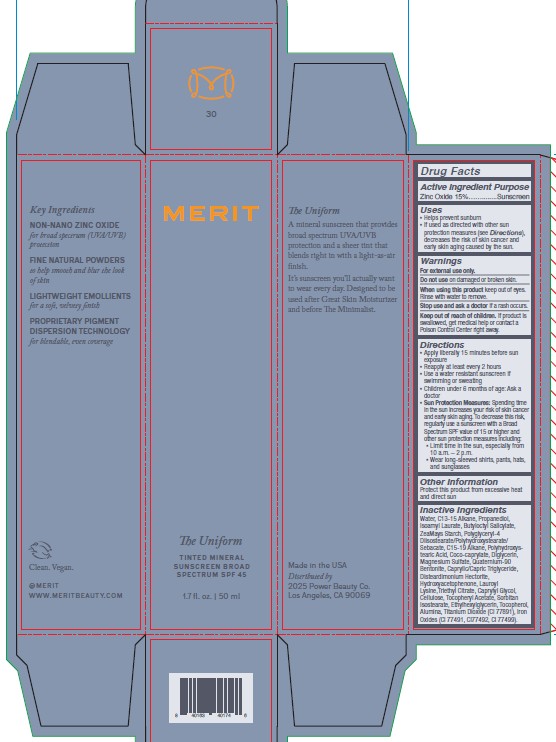 DRUG LABEL: MERIT The Uniform Tinted Mineral Sunscreen Broad Spectrum SPF 45
NDC: 85282-103 | Form: CREAM
Manufacturer: Power Beauty Co.
Category: otc | Type: HUMAN OTC DRUG LABEL
Date: 20250813

ACTIVE INGREDIENTS: ZINC OXIDE 15 g/100 mL
INACTIVE INGREDIENTS: ALUMINA; C13-15 ALKANE; POLYHYDROXYSTEARIC ACID (2300 MW); QUATERNIUM-90 BENTONITE; C15-19 ALKANE; POWDERED CELLULOSE; CI 77491; CI 77499; COCO-CAPRYLATE; POLYGLYCERIN-4; MAGNESIUM SULFATE; HYDROXYACETOPHENONE; LAUROYL LYSINE; ALPHA-TOCOPHEROL ACETATE; SORBITAN ISOSTEARATE; POLYGLYCERYL-4 DIISOSTEARATE/POLYHYDROXYSTEARATE/SEBACATE; PROPANEDIOL; GLYCERIN; CI 77891; WATER; ISOAMYL LAURATE; TRIETHYL CITRATE; CAPRYLYL GLYCOL; DISTEARDIMONIUM HECTORITE; BUTYLOCTYL SALICYLATE; CAPRYLIC/CAPRIC TRIGLYCERIDE; ZEA MAYS (CORN) STARCH; DIGLYCERIN; ETHYLHEXYLGLYCERIN; POLYGLYCERIN-3; TOCOPHEROL; CI 77492

MERIT The Uniform Tinted Mineral Sunscreen Broad Spectrum SPF 45

ACTIVE INGREDIENT

Active Ingredient | Purpose
Zince Oxide 15% | Sunscreen

Uses

- Helps prevent sunburn
- If used as directed with other sun protection measures (see Directions), decreases the risk of skin cancer and early signs of aging caused by the sun.

Warnings

For external use only.

Do not use on damaged or broken skin.

When using this product keep out of eyes. Rinse with warm water to remove.

Stop use and ask a doctor if a rash occurs.

Keep out of reach of children. If product is swallowed, get medical help or contact a Poison Control Center right away.

Directions

- Apply liberally 15 minutes before sun exposure
- Reapply at least every 2 hours
- Use a water resistant sunscreen if swimming or sweating
- Children under 6 months of age: Ask a doctor
- Sun Protection Measures: Spending time in the sun increases your risk of skin cancer and early skin aging. To decrease this risk, regularly use a sunscreen with a Broad Spectrum SPF value fo 15 or higher and other sun protection measures including: Limit the time in the sun, especially from 10 a.m. - 2 p.m. Wear long-sleeved shirts, pants, hats, and sunglasses.

Other Information

Protect this product from excessive heat and direct sun.

Inactive Ingredients

Water, Propanediol, C13-15 Alkane, Isoamyl Laurate, Butyloctyl Salicylate, Zea Mays (Corn) Starch, Polyglyceryl-4 Diisostearate/Polyhydroxystearate/Sebacate, C15-19 Alkane, Coco-Caprylate, Polyhydroxystearic Acid, Magnesium Sulfate, Diglycerin, Caprylic/Capric Triglyceride, Quaternium-90 Bentonite, Hydroxyacetophenone, Disteardimonium Hectorite, Lauroyl Lysine, Triethyl Citrate, Caprylyl Glycol, Tocopheryl Acetate, Sorbitan Isostearate, Cellulose, Ethylhexylglycerin, Polyglycerin-3, Polyglycerin-4, Glycerin, Tocopherol, Titanium Dioxide (CI 77891), Iron Oxides (CI 77491, CI 77492, CI 77499).

PRINCIPAL DISPLAY PANEL - 50 mL Carton - Shade 02

MERIT

The Uniform

Tinted Mineral

Sunscreen Broad

Spectrum SPF 45

1.7 fl. oz. | 50 ml

Shade 02

PRINCIPAL DISPLAY PANEL - 50 mL Carton - Shade 04

MERIT

The Uniform

Tinted Mineral

Sunscreen Broad

Spectrum SPF 45

1.7 fl. oz. | 50 ml

Shade 04

PRINCIPAL DISPLAY PANEL - 50 mL Carton - Shade 06

MERIT

The Uniform

Tinted Mineral

Sunscreen Broad

Spectrum SPF 45

1.7 fl. oz. | 50 ml

Shade 06

PRINCIPAL DISPLAY PANEL - 50 mL Carton - Shade 08

MERIT

The Uniform

Tinted Mineral

Sunscreen Broad

Spectrum SPF 45

1.7 fl. oz. | 50 ml

Shade 08

PRINCIPAL DISPLAY PANEL - 50 mL Carton - Shade 10

MERIT

The Uniform

Tinted Mineral

Sunscreen Broad

Spectrum SPF 45

1.7 fl. oz. | 50 ml

Shade 10

PRINCIPAL DISPLAY PANEL - 50 mL Carton - Shade 12

MERIT

The Uniform

Tinted Mineral

Sunscreen Broad

Spectrum SPF 45

1.7 fl. oz. | 50 ml

Shade 12

PRINCIPAL DISPLAY PANEL - 50 mL Carton - Shade 14

MERIT

The Uniform

Tinted Mineral

Sunscreen Broad

Spectrum SPF 45

1.7 fl. oz. | 50 ml

Shade 14

PRINCIPAL DISPLAY PANEL - 50 mL Carton - Shade 16

MERIT

The Uniform

Tinted Mineral

Sunscreen Broad

Spectrum SPF 45

1.7 fl. oz. | 50 ml

Shade 16

PRINCIPAL DISPLAY PANEL - 50 mL Carton - Shade 18

MERIT

The Uniform

Tinted Mineral

Sunscreen Broad

Spectrum SPF 45

1.7 fl. oz. | 50 ml

Shade 18

PRINCIPAL DISPLAY PANEL - 50 mL Carton - Shade 20

MERIT

The Uniform

Tinted Mineral

Sunscreen Broad

Spectrum SPF 45

1.7 fl. oz. | 50 ml

Shade 20

PRINCIPAL DISPLAY PANEL - 50 mL Carton - Shade 22

MERIT
The Uniform

Tinted Mineral

Sunscreen Broad

Spectrum SPF 45

1.7 fl. oz. | 50 ml

Shade 22

PRINCIPAL DISPLAY PANEL - 50 mL Carton - Shade 24

MERIT

The Uniform

Tinted Mineral

Sunscreen Broad

Spectrum SPF 45

1.7 fl. oz. | 50 ml

Shade 24

PRINCIPAL DISPLAY PANEL - 50 mL Carton - Shade 26

MERIT

The Uniform

Tinted Mineral

Sunscreen Broad

Spectrum SPF 45

1.7 fl. oz. | 50 ml

Shade 26

PRINCIPAL DISPLAY PANEL - 50 mL Carton - Shade 28

MERIT

The Uniform

Tinted Mineral

Sunscreen Broad

Spectrum SPF 45

1.7 fl. oz. | 50 ml

Shade 28

PRINCIPAL DISPLAY PANEL - 50 mL Carton - Shade 30

MERIT

The Uniform

Tinted Mineral

Sunscreen Broad

Spectrum SPF 45

1.7 fl. oz. | 50 ml

Shade 30